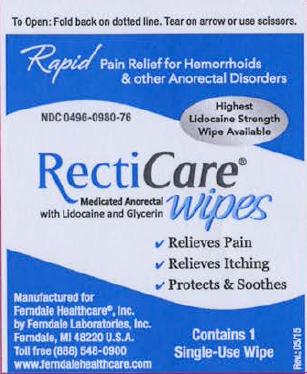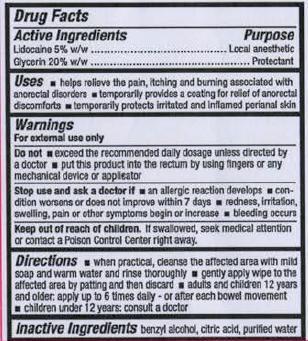 DRUG LABEL: RECTICARE
NDC: 0496-0980 | Form: CLOTH
Manufacturer: Ferndale Laboratories, Inc.
Category: otc | Type: HUMAN OTC DRUG LABEL
Date: 20241217

ACTIVE INGREDIENTS: LIDOCAINE 50 mg/1 g; GLYCERIN 200 mg/1 g
INACTIVE INGREDIENTS: BENZYL ALCOHOL; ANHYDROUS CITRIC ACID; WATER

RectiCare Medicated Anorectal Wipes

Active Ingredients

Lidocaine 5% w/w

Glycerin 20% w/w

Purpose

Lidocaine 5% w/w........................................Local anesthetic

Glycerin 20% w/w.........................................Protectant

Uses

- helps relieve the pain, itching and burning associated with anorectal disorders
- temporarily provides a coating for relief of anorectal discomforts
- temporarily protects irritated and inflamed perianal skin

Warnings

For external use only

Do not

- exceed the recommended daily dosage unless directed by a doctor
- put this product into the rectum by using fingers or any mechanical device or applicator

Stop use and ask a doctor if

- an allergic reaction develops
- condition worsens or does not improve witin 7 days
- redness, irriation, swelling, pain or other symptoms begin or increase
- bleeding occurs

Keep out of reach of children. If swallowed, seek medical attention or contact a Poison Control Center right away.

Directions

- when practical, cleanse the affected area with mild soap and warm water and rinse thoroghly
- gently apply wipe to the affected area by patting and then discard
- adults and children 12 years & older: apply up to 6 times daily - or after each bowel movement
- children under 12 years: consult a doctor

Inactive Ingredients

benzyl alcohol, citric acid, purified water